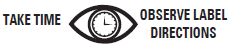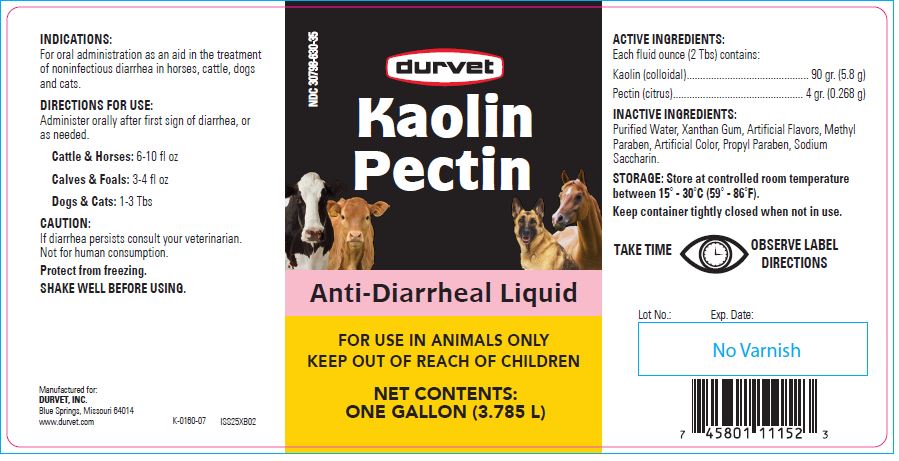 DRUG LABEL: Kaolin Pectin
NDC: 30798-630 | Form: SUSPENSION
Manufacturer: Durvet, Inc.
Category: animal | Type: OTC ANIMAL DRUG LABEL
Date: 20250512

ACTIVE INGREDIENTS: KAOLIN 208.1 g/1 L; PECTIN, CITRUS 8.8 g/1 L

Kaolin
Pectin

PURPOSE

Anti-Diarrheal Liquid

KEEP OUT OF REACH OF CHILDREN

FOR USE IN ANIMALS ONLY
KEEP OUT OF REACH OF CHILDREN

NET CONTENTS:

ONE GALLON (3.785 L)

INDICATIONS:

For oral administration as an aid in the treatment of noninfectious diarrhea in horses, cattle, dogs and cats.

DIRECTIONS FOR USE:

Administer orally after first sign of diarrhea and after each loose bowel movement, or as needed.
Cattle & Horses: 6-10 fl oz
Calves & Foals: 3-4 fl oz
Dogs & Cats: 1-3 Tbs

CAUTION:

If diarrhea persists consult your veterinarian.
Not for human consumption.
Protect from freezing.
SHAKE WELL BEFORE USING.

ACTIVE INGREDIENTS:

Each fluid ounce (2 Tbs) contains:
Kaolin (colloidal)............................................. 90 gr. (5.8 g)
Pectin (citrus)................................................ 4 gr. (0.268 g)

INACTIVE INGREDIENTS:

Purified Water, Xanthan Gum, Artificial Flavors, Methyl Paraben, Artificial Color, Propyl Paraben, Sodium Saccharin.

STORAGE:

Store at controlled room temperature between 15º to 30ºC (59º-86ºF).

Keep container tightly closed when not in use.

INFORMATION FOR OWNERS/CAREGIVERS

Manufactured for:
DURVET, INC.
Blue Springs, Missouri 64014
www.durvet.com ISS25XB02